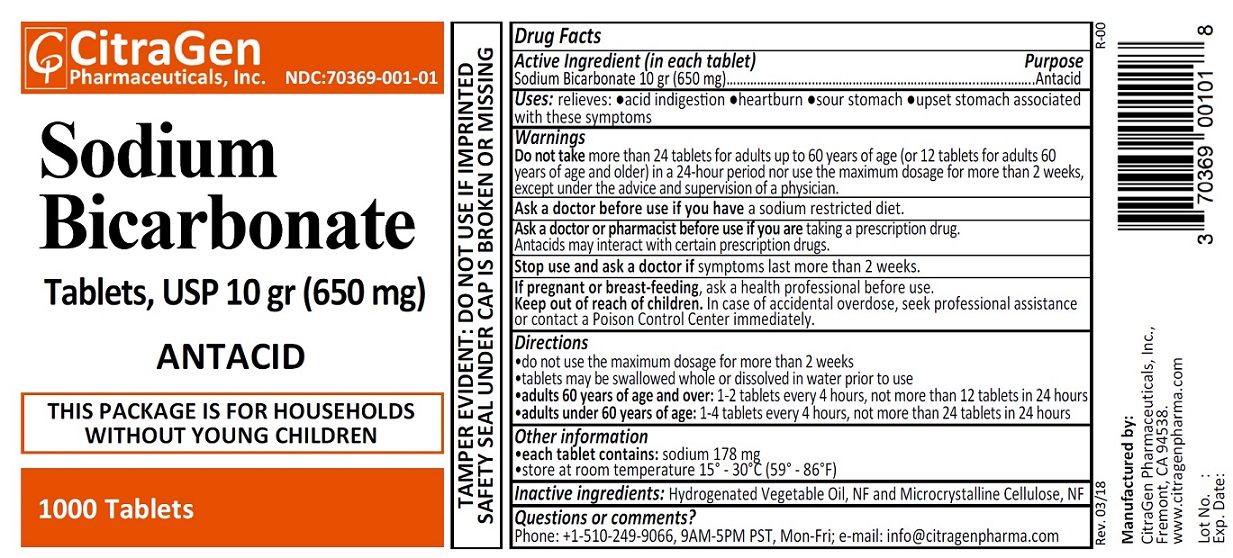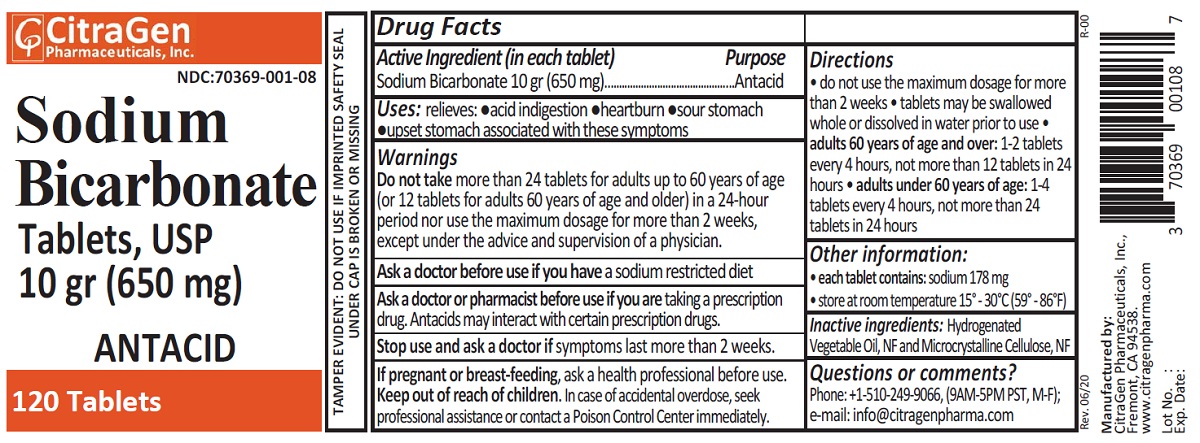 DRUG LABEL: Sodium Bicarbonate
NDC: 70369-001 | Form: TABLET
Manufacturer: CitraGen Pharmaceuticals Inc.
Category: otc | Type: HUMAN OTC DRUG LABEL
Date: 20250130

ACTIVE INGREDIENTS: SODIUM BICARBONATE 650 mg/1 1
INACTIVE INGREDIENTS: HYDROGENATED COTTONSEED OIL; CELLULOSE, MICROCRYSTALLINE

Sodium Bicarbonate Tablets, USP 10gr (650 mg)

Drug Facts

Active ingredient (in each tablet)

Sodium Bicarbonate 10 gr (650 mg)

Purpose

Antacid

Uses

relieves:

- acid indigestion
- heartburn
- sour stomach
- upset stomach associated with these symptoms

Warnings

Do not take more than 24 tablets for adults up to 60 years of age (or 12 tablets for adults 60 years of age and older) in a 24-hour period nor use the maximum dosage for more than 2 weeks, except under the advice and supervision of a physician.

Ask a doctor before use if you have a sodium restricted diet.

Ask a doctor or pharmacist before use if you are taking a prescription drug.

Antacids may interact with certain prescription drugs.

Stop use and ask a doctor if symptoms last more than 2 weeks.

PREGNANCY OR BREAST FEEDING

If pregnant or breast-feeding, ask a health professional before use.

Keep out of reach of children.

OVERDOSAGE

In case of accidental overdose, seek professional assistance or contact a Poison Control Center immediately.

Directions

- do not use the maximum dosage for more than 2 weeks
- tablets may be swallowed whole or dissolved in water prior to use
- adults 60 years of age and over: 1-2 tablets every 4 hours, not more than 12 tablets in 24 hours
- adults under 60 years of age: 1-4 tablets every 4 hours, not more than 24 tablets in 24 hours

Other information

each tablet contains: sodium 178 mg

store at room temperature 15º - 30º C (59º - 86º F)

Inactive ingredients

Hydrogenated Vegetable Oil, NF and Microcrystalline Cellulose, NF

Questions or comments?

Phone: +1-510-249-9066 (9AM-5PM PST, Mon-Fri); e-mail: info@citragenpharma.com

TAMPER EVIDENT: DO NOT USE IF IMPRINTED SAFETY SEAL UNDER CAP IS BROKEN OR MISSING

Manufactured by:
CitraGen Pharmaceuticals, Inc.,
Fremont, CA 94538.

www.citragenpharma.com

Rev. 03/18 R-00

PACKAGE LABEL

CitraGen Pharmaceuticals, Inc.

NDC: 70369-001-01

Sodium Bicarbonate Tablets, USP 10 gr (650 mg)

ANTACID

1000 Tablets

THIS PACKAGE IS FOR HOUSEHOLDS WITHOUT YOUNG CHILDREN

PACKAGE LABEL

CitraGen Pharmaceuticals, Inc.

NDC: 70369-001-08

Sodium Bicarbonate Tablets, USP 10 gr (650 mg)

ANTACID

120 Tablets